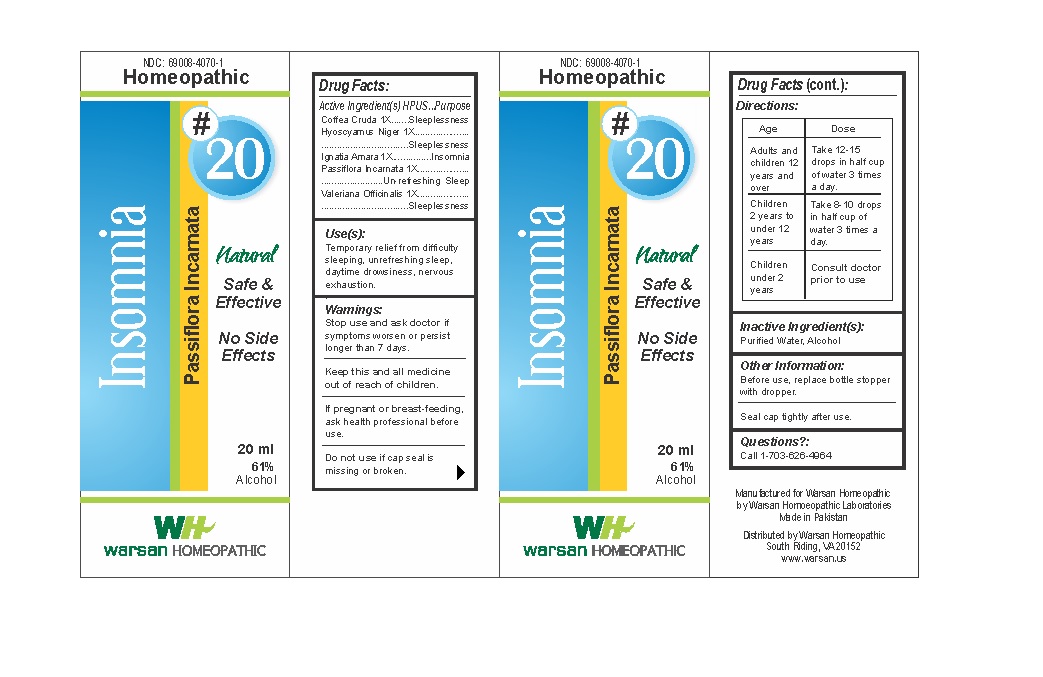 DRUG LABEL: Combination Remedy 20 - Insomnia
NDC: 69008-4070 | Form: SOLUTION/ DROPS
Manufacturer: Warsan Homoeopathic Laboratories
Category: homeopathic | Type: HUMAN OTC DRUG LABEL
Date: 20171225

ACTIVE INGREDIENTS: STRYCHNOS IGNATII SEED 1 [hp_X]/1 mL; PASSIFLORA INCARNATA FLOWERING TOP 1 [hp_X]/1 mL; ARABICA COFFEE BEAN 1 [hp_X]/1 mL; HYOSCYAMUS NIGER 1 [hp_X]/1 mL; VALERIAN 1 [hp_X]/1 mL
INACTIVE INGREDIENTS: ALCOHOL; WATER

Stop use and ask doctor if symptoms worsen or persist longer than 7 days.

If pregnant or breast-feeding, ask health professional before use.

Do not use if tamper evident seal is missing or broken.

Keep out of reach of children.

ACTIVE INGREDIENT

Coffea Cruda 1X

Hyoscyamus Niger 1X

Ignatia Amara 1X

Passiflora Incarnata 1X

Valeriana Officinalis 1x

PURPOSE

Temporary relief from difficulty sleeping, unrefreshing sleep, daytime drowsiness, nervous exhaustion.

INACTIVE INGREDIENT

Purified Water

Alcohol

DOSAGE AND ADMINISTRATION

Adults and children 12 years and older: Take 10-15 drops in half cup of water 3 times a day.

Children 2 years to under 12 years: Take 8-10 drops in half cup of water of 3 times a day.

Children under 2 years: Consult doctor prior to use.

INDICATIONS AND USAGE

Temporary relief from difficulty sleeping, unrefreshing sleep, daytime drowsiness, nervous exhaustion.